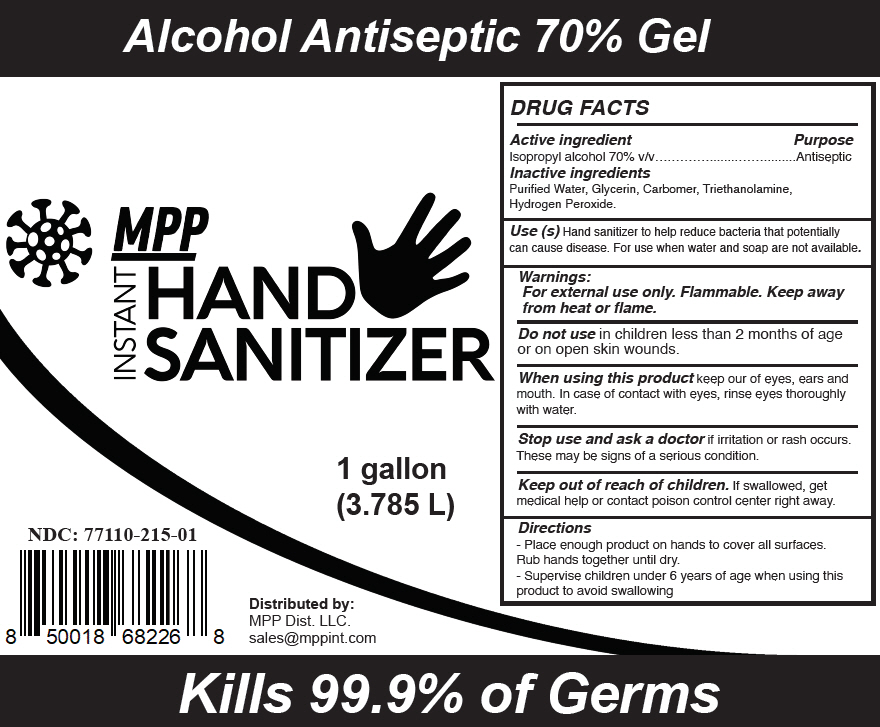 DRUG LABEL: MPP INSTANT HAND SANITIZER
NDC: 77110-215 | Form: GEL
Manufacturer: Biominerales Pharma
Category: otc | Type: HUMAN OTC DRUG LABEL
Date: 20200723

ACTIVE INGREDIENTS: ISOPROPYL ALCOHOL 70 mL/100 mL
INACTIVE INGREDIENTS: WATER; GLYCERIN; CARBOMER HOMOPOLYMER, UNSPECIFIED TYPE; TROLAMINE; HYDROGEN PEROXIDE

MPP INSTANT HAND SANITIZER

DRUG FACTS

Active ingredient

Isopropyl alcohol 70% v/v

Purpose

Antiseptic

Inactive ingredients

Purified Water, Glycerin, Carbomer, Triethanolamine, Hydrogen Peroxide.

Use (s)

Hand sanitizer to help reduce bacteria that potentially can cause disease. For use when water and soap are not available.

Warnings

For external use only. Flammable. Keep away from heat or flame.

Do not use in children less than 2 months of age or on open skin wounds.

When using this product keep our of eyes, ears and mouth. In case of contact with eyes, rinse eyes thoroughly with water.

Stop use and ask a doctor if irritation or rash occurs. These may be signs of a serious condition.

Keep out of reach of children. If swallowed, get medical help or contact poison control center right away.

Directions

- Place enough product on hands to cover all surfaces. Rub hands together until dry.
- Supervise children under 6 years of age when using this product to avoid swallowing

Distributed by:
MPP Dist. LLC.
sales@mppint.com

PRINCIPAL DISPLAY PANEL - 3.785 L Bottle Label

Alcohol Antiseptic 70% Gel

MPP
INSTANT
HAND
SANITIZER

1 gallon
(3.785 L)

NDC: 77110-215-01

Distributed by:
MPP Dist. LLC.
sales@mppint.com

Kills 99.9% of Germs